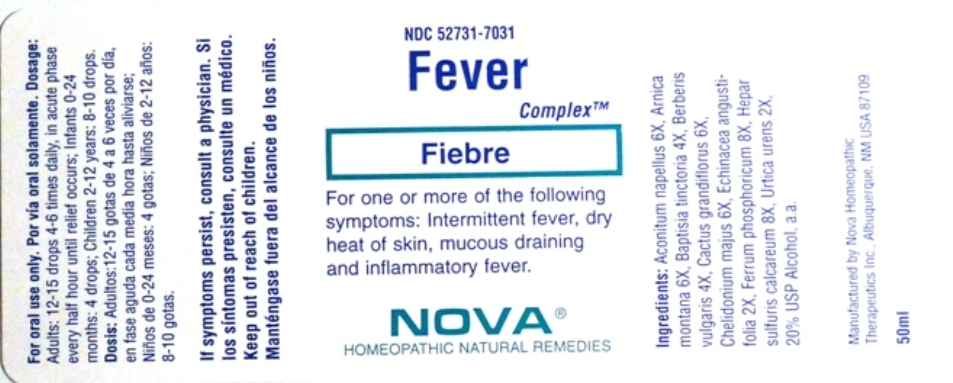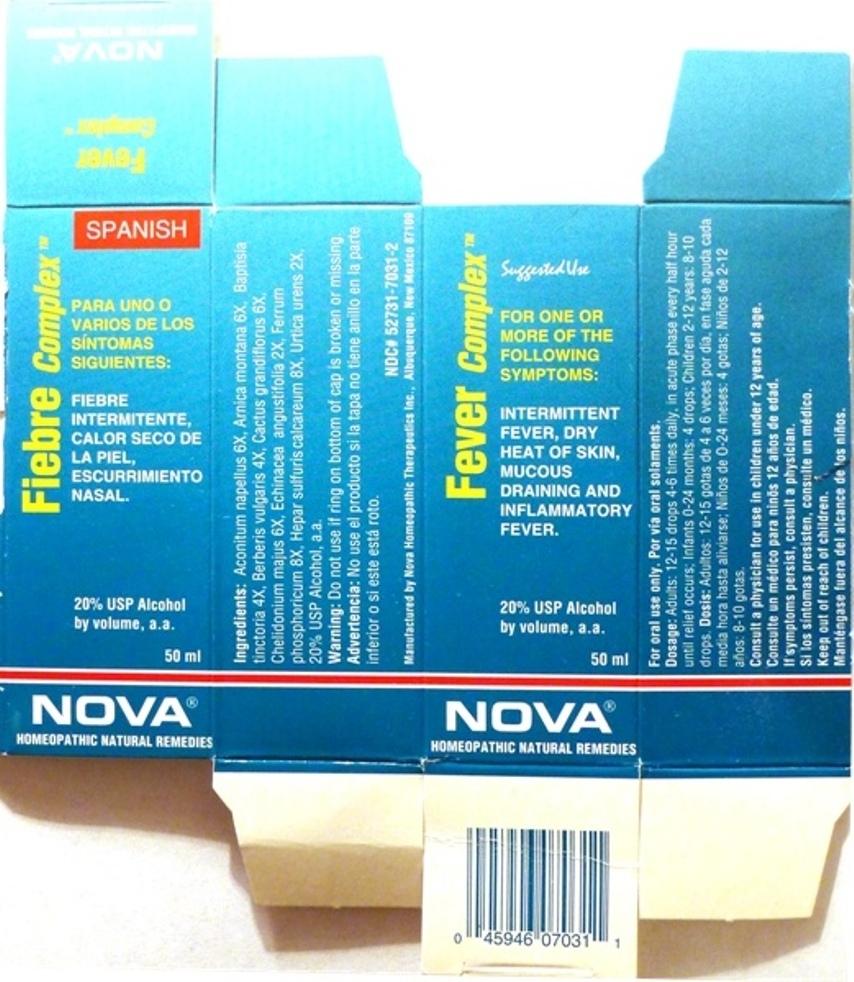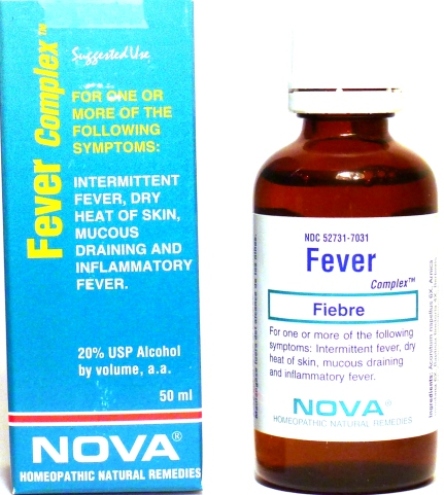 DRUG LABEL: Fever Complex
NDC: 52731-7031 | Form: LIQUID
Manufacturer: Nova Homeopathic Therapeutics, Inc.
Category: homeopathic | Type: HUMAN OTC DRUG LABEL
Date: 20110601

ACTIVE INGREDIENTS: ACONITUM NAPELLUS 6 [hp_X]/1 mL; ARNICA MONTANA 6 [hp_X]/1 mL; BAPTISIA TINCTORIA ROOT 4 [hp_X]/1 mL; BERBERIS VULGARIS ROOT BARK 4 [hp_X]/1 mL; SELENICEREUS GRANDIFLORUS STEM 6 [hp_X]/1 mL; CHELIDONIUM MAJUS 6 [hp_X]/1 mL; ECHINACEA ANGUSTIFOLIA 2 [hp_X]/1 mL; FERRUM PHOSPHORICUM 8 [hp_X]/1 mL; CALCIUM SULFIDE 8 [hp_X]/1 mL; URTICA URENS 2 [hp_X]/1 mL
INACTIVE INGREDIENTS: ALCOHOL

Fever Complex

Purpose:

Suggested use for one or more of the following symptoms:

Intermittent fever, dry heat of skin, mucous draining and inflammatory fever.

Usage and Dosage:

For oral use only.

DOSAGE AND ADMINISTRATION

Adults:
In Acute Phase:
12-15 drops, every half hour until relief occurs
When Relief Occurs:
12-15 drops, 4-6 times per day
Children 2-12 years:
8-10 drops, 4-6 times per day
Infants 0-24 months:
4 drops, 4-6 times per day

Warnings:

Keep out of reach of children.

WARNINGS

If symptoms persist, consult a physician.
Do not use if ring on bottom of cap is broken or missing.

Active Ingredients:

Aconitum napellus 6X, Arnica montana 6X, Baptisia tinctoria 4X, Berberis vulgaris 4X, Cactus grandiflorus 6X,
Chelidonium majus 6X, Echinacea angustifolia 2X, Ferrum phosphoricum 8X, Hepar sulfuris calcareum 8X, Urtica urens 2X

Inactive Ingredients:

Alcohol, 20% USP

QUESTIONS

Manufactured by Nova Homeopathic Therapeutics Inc., Albuquerque, New Mexico USA 87109
1-800-225-8094

PACKAGE LABEL

Fever Complex Product

Fever Complex Bottle Label

Fever Complex Box